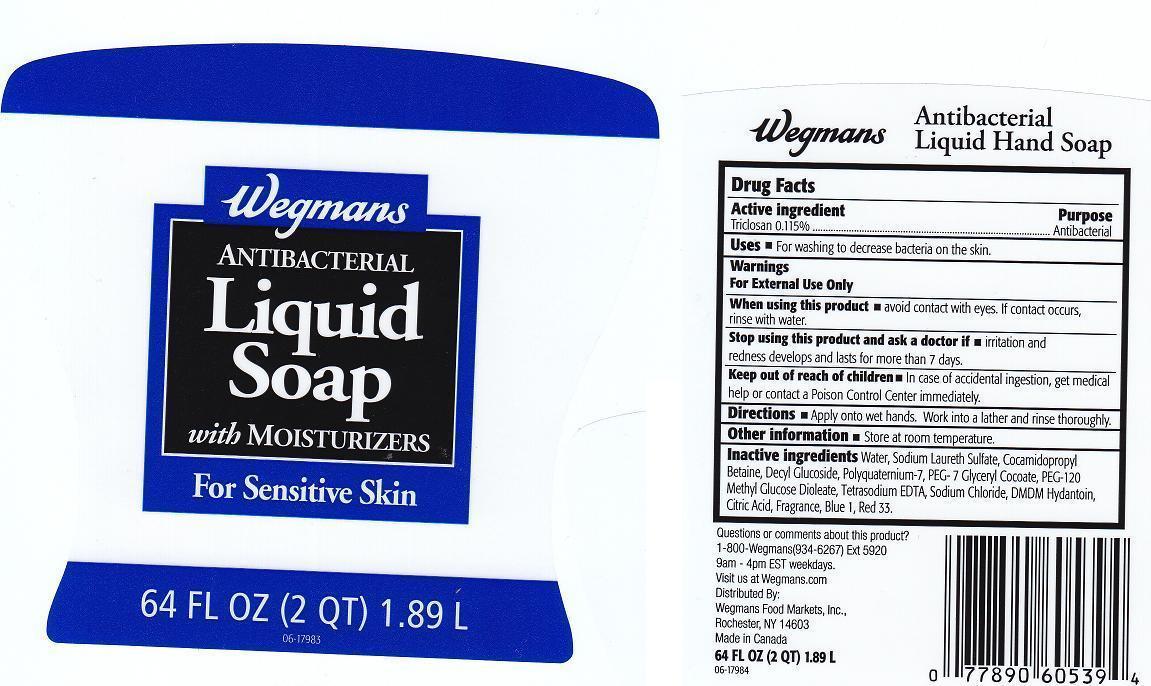 DRUG LABEL: WEGMANS
NDC: 47124-721 | Form: LIQUID
Manufacturer: WEGMANS FOOD MARKETS INC.
Category: otc | Type: HUMAN OTC DRUG LABEL
Date: 20130401

ACTIVE INGREDIENTS: TRICLOSAN 1.15 mg/1 mL
INACTIVE INGREDIENTS: WATER; SODIUM LAURETH SULFATE; COCAMIDOPROPYL BETAINE; DECYL GLUCOSIDE; POLYQUATERNIUM-7 (70/30 ACRYLAMIDE/DADMAC; 1600000 MW); PEG-7 GLYCERYL COCOATE; PEG-120 METHYL GLUCOSE DIOLEATE; EDETATE SODIUM; SODIUM CHLORIDE; DMDM HYDANTOIN; CITRIC ACID MONOHYDRATE; FD&C BLUE NO. 1; D&C RED NO. 33

DRUG FACTS

ACTIVE INGREDIENT

TRICLOSAN 0.115%

PURPOSE

ANTIBACTERIAL

USES

FOR WASHING TO DECREASE BACTERIA ON THE SKIN.

WARNINGS

FOR EXTERNAL USE ONLY.

WHEN USING THIS PRODUCT

AVOID CONTACT WITH EYES. IF CONTACT OCCURS, RINSE WITH WATER.

STOP USING THIS PRODUCT AND ASK A DOCTOR IF

IRRITATION AND REDNESS DEVELOPS AND LASTS FOR MORE THAN 7 DAYS.

KEEP OUT OF REACH OF CHILDREN

IN CASE OF ACCIDENTAL INGESTION, GET MEDICAL HELP OR CONTACT A POISON CONTROL CENTER IMMEDIATELY.

DIRECTIONS

APPLY ONTO WET HANDS. WORK INTO A LATHER AND RINSE THOROUGHLY.

OTHER INFORMATION

STORE AT ROOM TEMPERATURE.

INACTIVE INGREDIENTS

WATER, SODIUM LAURETH SULFATE, COCAMIDOPROPYL BETAINE, DECYL GLUCOSIDE, POLYQUATERNIUM-7, PEG-7 GLYCERYL COCOATE, PEG-120 METHYL GLUCOSE DIOLEATE, TETRASODIUM EDTA, SODIUM CHLORIDE, DMDM HYDANTOIN, CITRIC ACID, FRAGRANCE, BLUE 1, RED 33.